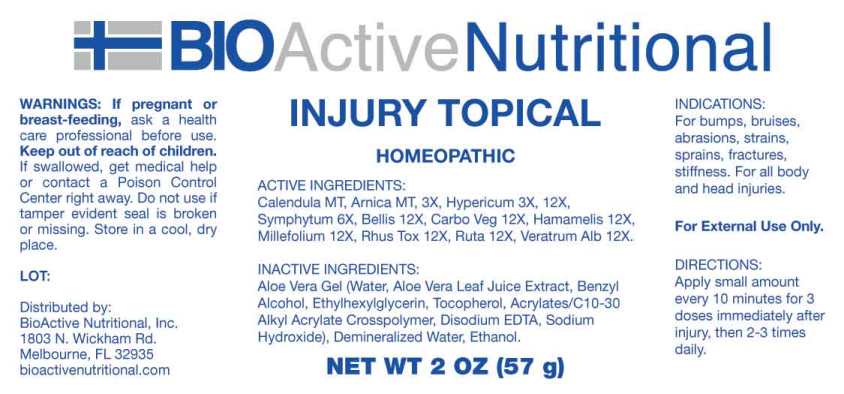 DRUG LABEL: Injury Topical
NDC: 43857-0608 | Form: LOTION
Manufacturer: BioActive Nutritional, Inc.
Category: homeopathic | Type: HUMAN OTC DRUG LABEL
Date: 20241017

ACTIVE INGREDIENTS: CALENDULA OFFICINALIS FLOWERING TOP 1 [hp_X]/1 g; ARNICA MONTANA WHOLE 1 [hp_X]/1 g; HYPERICUM PERFORATUM WHOLE 3 [hp_X]/1 g; COMFREY ROOT 6 [hp_X]/1 g; BELLIS PERENNIS WHOLE 12 [hp_X]/1 g; ACTIVATED CHARCOAL 12 [hp_X]/1 g; HAMAMELIS VIRGINIANA ROOT BARK/STEM BARK 12 [hp_X]/1 g; ACHILLEA MILLEFOLIUM WHOLE 12 [hp_X]/1 g; TOXICODENDRON PUBESCENS LEAF 12 [hp_X]/1 g; RUTA GRAVEOLENS FLOWERING TOP 12 [hp_X]/1 g; VERATRUM ALBUM ROOT 12 [hp_X]/1 g
INACTIVE INGREDIENTS: WATER; ALOE VERA LEAF; BENZYL ALCOHOL; ETHYLHEXYLGLYCERIN; TOCOPHEROL; CARBOMER INTERPOLYMER TYPE A (ALLYL SUCROSE CROSSLINKED); EDETATE DISODIUM ANHYDROUS; SODIUM HYDROXIDE; ALCOHOL

DRUG FACTS:

ACTIVE INGREDIENTS:

Calendula Officinalis MT, Arnica Montana MT, 3X, Hypericum Perforatum 3X, 12X, Symphytum Officinale 6X, Bellis Perennis 12X, Carbo Vegetabilis 12X, Hamamelis Virginiana 12X, Millefolium 12X, Rhus Tox 12X, Ruta Graveolens 12X, Veratrum Album 12X.

INDICATIONS:

For bumps, bruises, abrasions, strains, sprains, fractures, stiffness. For all body and head injuries.

WARNINGS:

If pregnant or breast-feeding, ask a health care professional before use.

Keep out of reach of children. If swallowed, get medical help or contact a Poison Control Center right away.

Do not use if tamper evident seal is broken or missing.

Store in a cool, dry place.

For External Use Only.

Keep out of reach of children. If swallowed, get medical help or contact a Poison Control Center right away.

DIRECTIONS:

Apply small amount every 10 minutes for 3 doses immediately after injury, then 2-3 times daily.

INDICATIONS:

For bumps, bruises, abrasions, strains, sprains, fractures, stiffness. For all body and head injuries.

INACTIVE INGREDIENTS:

Water, Aloe Vera Leaf Juice Extract, Benzyl alcohol, Ethylhexylglycerin, Tocopherol, Acrylates/C10-30 Alkyl Acrylate Crosspolymer, Disodium EDTA, Sodium Hydroxide, Ethanol 3.6%.

QUESTIONS:

Distributed by:
BioActive Nutritional, Inc.
1803 N. Wickham Rd.
Melbourne, FL 32935
bioactivenutritional.com

PACKAGE LABEL DISPLAY:

BIOActive Nutritional

INJURY TOPICAL

HOMEOPATHIC

NET WT 2 OZ (57 g)